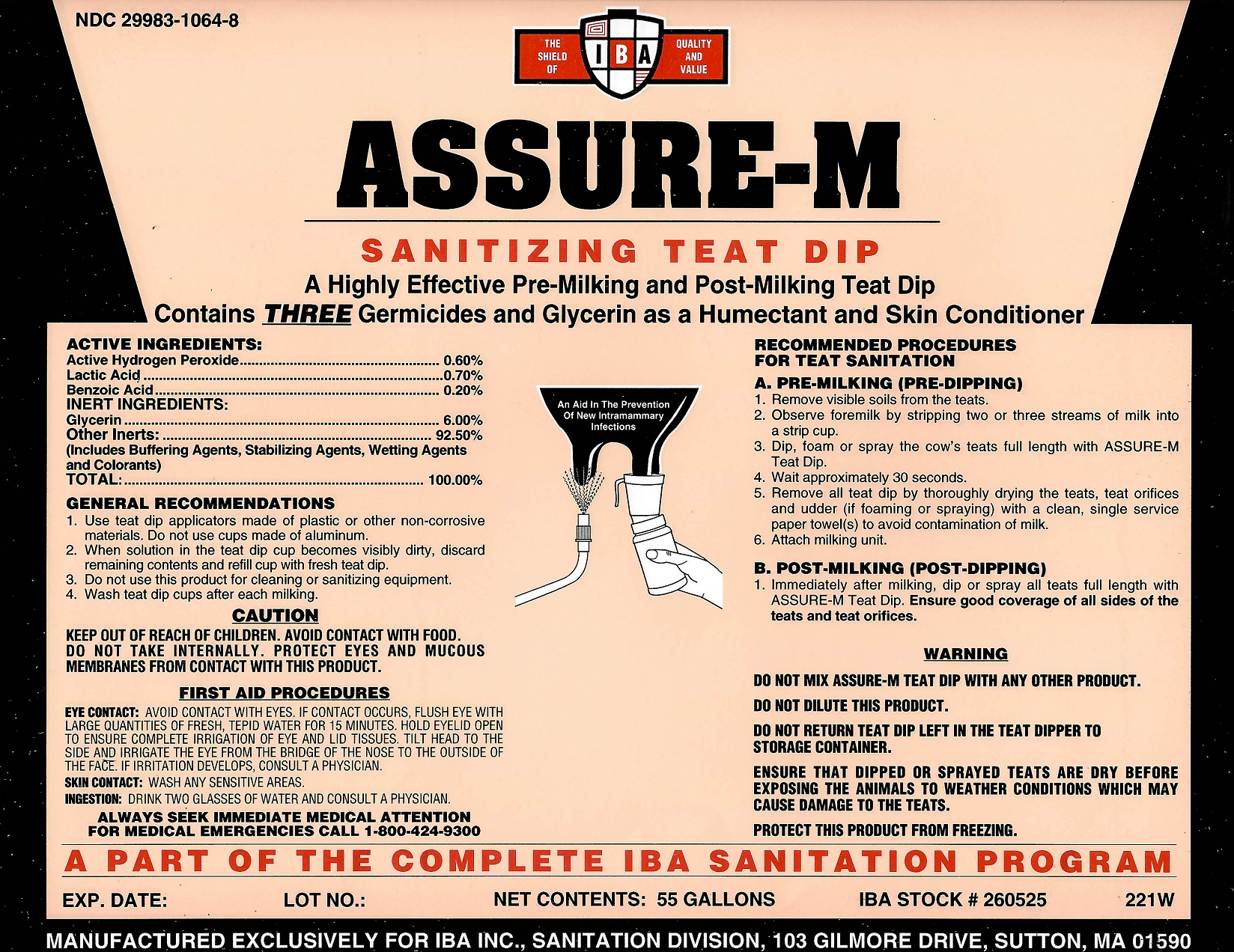 DRUG LABEL: ASSURE-M
NDC: 29983-1064 | Form: LIQUID
Manufacturer: IBA
Category: animal | Type: OTC ANIMAL DRUG LABEL
Date: 20251126

ACTIVE INGREDIENTS: HYDROGEN PEROXIDE 0.60 kg/100 kg; LACTIC ACID 0.70 kg/100 kg; BENZOIC ACID 0.20 kg/100 kg

Assure-M

ACTIVE INGREDIENTS

Active Hydrogen Peroxide...........0.60%
Lactic Acid……………………….…………0.70%
Benzoic Acid...............................0.20%

INERT INGREDIENTS

Glycerin..........................................6.00%
Other Inerts:................................92.50%
(includes Buffering Agents, Stabilizing Agents, Wetting Agents and Colorants)
TOTAL.................100%

GENERAL RECOMMENDATIONS

1. Use teat dip applicators made of plastic or other non-corrosive materials. Do not use cups made of aluminum.
2. When solution in the teat dip cup becomes visibly dirty, discard remaining contents and refill cup with fresh teat dip.
3. Do not use this product for cleaning or sanitizing equipment.
4. Wash Teat Dip cups after each milking.

CAUTION

KEEP OUT OF REACH OF CHILDREN

AVOID CONTACT WITH FOOD. DO NOT TAKE INTERNALLY.

PROTECT EYES AND MUCOUS MEMBRANES FROM CONTACT WITH THIS PRODUCT. FIRST AID PROCEDURES

EYE CONTACT: IMMEDIATELY FLUSH EYE WITH LARGE AMOUNTS OF FRESH, TEPID WATER FOR 15 MINUTES. HOLD EYELID OPEN TO ENSURE COMPLETE IRRIGATION OF EYE AND LID TISSUES. TILT HEAD TO THE SIDE AND IRRIGATE THE EYE FROM THE BRIDGE OF THE NOSE TO THE OUTSIDE OF THE FACE. IF IRRITAITION DEVELOPS CONSULT A PHYSICIAN.
SKIN CONTACT: WASH ANY SENSITIVE AREAS.
INGESTION: DRINK TWO GLASSES OF WATER AND CONSULT A PHYSICIAN
ALWAYS SEEK IMMEDIATE MEDICAL ATTENTION
FOR MEDICAL EMERGENCIES CALL 1-800-424-9300

RECOMMENDED PROCEDURES FOR TEAT SANITATION:

A. PRE-MILKING (PRE-DIPPING)
1. Remove visible soils from the teats.
2. Observe formilk by stripping two or three streams of milk into a strip cup.
3. Dip or spray the cow's teats full length with ASSURE-M Teat Dip.
4. Wait approximately 30 seconds.
5. Remove all teat dip by thoroughly drying the teats and teat orifices and udder (if foaming or spraying) with a clean, single service paper towels(s).
6. Attach milking unit.
B. POST-MILKING (POST-DIPPING)
1. Immediately after milking, dip or spray all teats full length with ASSURE-M Teat Dip. Ensure good coverage of all sides of the teats and teat orifices.
A PART OF THE COMPLETE IBA SANITATION PROGRAM

WARNING
DO NOT MIX ASSURE-M WITH ANY OTHER PRODUCT.
DO NOT DILUTE PRODUCT.
DO NOT RETURN TEAT DIP LEFT IN THE TEAT DIPPER TO STORAGE CONTAINER.
ENSURE THAT DIPPED OR SPRAYED TEATS ARE DRY BEFORE EXPOSING THE ANIMALS TO WEATHER CONDITIONS WHICH MAY CAUSE DAMAGE TO THE TEATS.

PROTECT THIS PRODUCT FROM FREEZING.